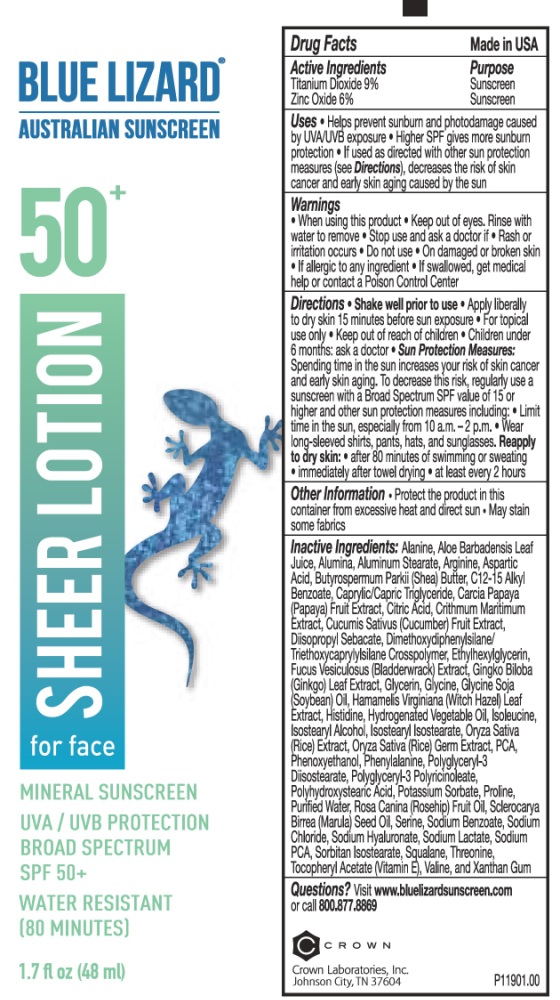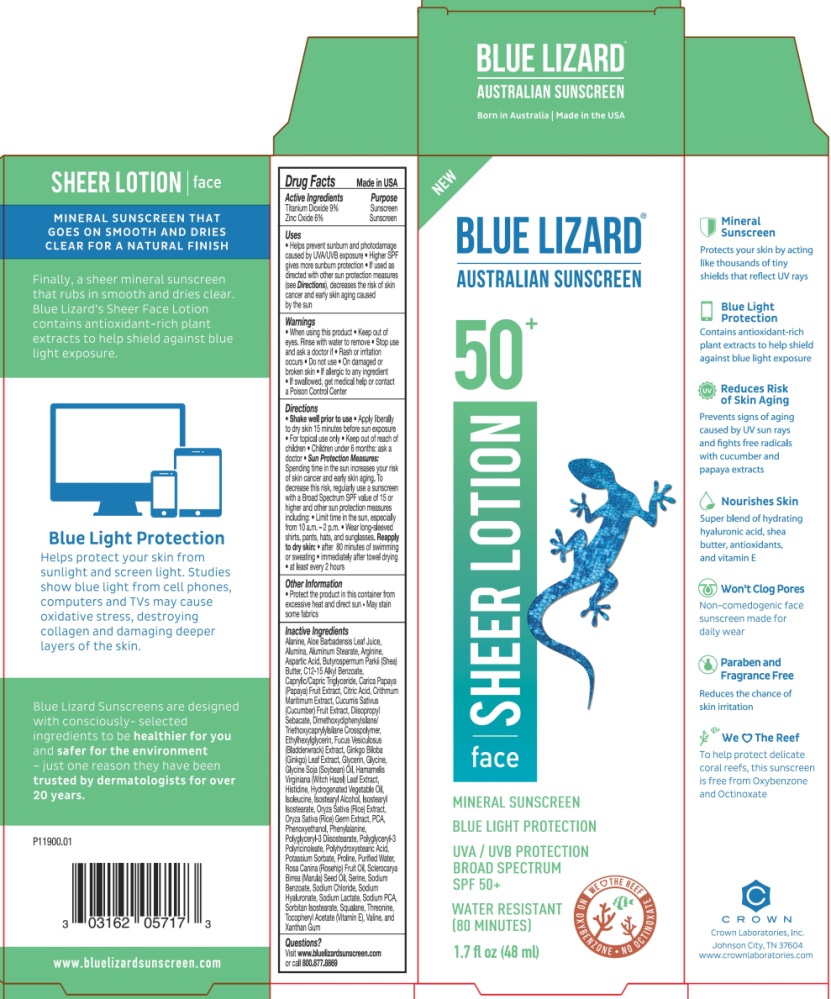 DRUG LABEL: Blue Lizard Sheer Face SPF 50 Sunscreen
NDC: 0316-2057 | Form: LOTION
Manufacturer: Crown Laboratories
Category: otc | Type: HUMAN OTC DRUG LABEL
Date: 20260112

ACTIVE INGREDIENTS: ZINC OXIDE 66.6 mg/1 mL; TITANIUM DIOXIDE 99.9 mg/1 mL
INACTIVE INGREDIENTS: SODIUM LACTATE; SODIUM PYRROLIDONE CARBOXYLATE; THREONINE; VALINE; XANTHAN GUM; SORBITAN ISOSTEARATE; .ALPHA.-TOCOPHEROL ACETATE; HYALURONATE SODIUM; WATER; SERINE; SODIUM BENZOATE; ALUMINUM STEARATE; ALUMINUM OXIDE; ISOSTEARYL ISOSTEARATE; FUCUS VESICULOSUS; GINKGO; GLYCERIN; GLYCINE; HISTIDINE; POLYGLYCERYL-3 PENTARICINOLEATE; HYDROGENATED RAPESEED OIL; SOYBEAN OIL; RICE GERM; PIDOLIC ACID; POLYGLYCERYL-3 DIISOSTEARATE; ASPARTIC ACID; ETHYLHEXYLGLYCERIN; SHEA BUTTER; PAPAYA; CRITHMUM MARITIMUM; ALOE VERA LEAF; CUCUMBER; PHENOXYETHANOL; PHENYLALANINE; ISOLEUCINE; ISOSTEARYL ALCOHOL; SQUALANE; SCLEROCARYA BIRREA SEED OIL; ROSA CANINA FRUIT OIL; PROLINE; SODIUM CHLORIDE; ALKYL (C12-15) BENZOATE; CITRIC ACID MONOHYDRATE; DIISOPROPYL SEBACATE; HAMAMELIS VIRGINIANA LEAF; TRIETHOXYCAPRYLYLSILANE; POTASSIUM SORBATE; DIMETHOXYDIPHENYLSILANE; POLYHYDROXYSTEARIC ACID (2300 MW); HYDROGENATED PALM OIL; ALANINE; ARGININE; MEDIUM-CHAIN TRIGLYCERIDES

Blue Lizard Sheer Face Lotion SPF 50 Sunscreen

Active Ingredients

Titanium Dioxide 9%

Zinc Oxide 6%

Purpose

Sunscreen

Uses

- Helps prevent sunburn and photodamage caused by UVA/UVB exposure
- Higher SPF gives more sunburn protection
- If used as directed with other sun protection measures (see Directions), decreases the risks of skin cancer and early skin aging caused by the sun

Warnings

• When using this product • Keep out of eyes. Rinse with water to remove

• Stop use and ask doctor if • Rash or irritation occurs

• Do not use • On damaged or broken skin • If allergic to any ingredient

• If swallowed, get medical help or contact a Poison Control Center

Directions

• Shake well prior to use

• Apply liberally to dry skin 15 minutes before sun exposure

• For topical use only

• Children under 6 months: ask a doctor

• Sun Protection Measures: Spending time in the sun increases your risk of skin cancer and early skin aging. To decrease this risk, regularly use a sunscreen with a Broad Spectrum SPF value of 15 or higher and other sun protection measures including: Limit time in the sun, especially from 10 a.m. - 2 p.m.

• Wear long-sleeved shirts, pants, hats, and sunglasses.

• Reapply to dry skin: • after 80 minutes of swimming or sweating • immediately after towel drying • at least every 2 hours

Other Information

- Protect the product in this container from excessive heat and direct sun
- May stain some fabrics

Inactive Ingredients

Alanine, Aloe Barbadensis Leaf Juice, Alumina, Aluminum Stearate, Arginine, Aspartic Acid, Butyrospermum Parkii (Shea) Butter, C12-15 Alkyl Benzoate, Caprylic/Capric Triglyceride, Carica Papaya (Papaya) Fruit Extract, Citric Acid, Crithmum Maritimum Extract, Cucumis Sativus (Cucumber) Fruit Extract, Diisopropyl Sebacate, Dimethoxydiphenylsilane/ Triethoxycaprylylsilane Crosspolymer, Ethylhexylglycerin, Fucus Vesiculosus (Bladderwrack) Extract, Ginkgo Biloba (Ginkgo) Leaf Extract, Glycerin, Glycine, Glycine Soja (Soybean) Oil, Hamamelis Virginiana (Witch Hazel) Leaf Extract, Histidine, Hydrogenated Vegetable Oil, Isoleucine, Isostearyl Alcohol, Isostearyl Isostearate, Oryza Sativa (Rice) Extract, Oryza Sativa (Rice) Germ Extract, PCA, Phenoxyethanol, Phenylalanine, Polyglyceryl-3 Diisostearate, Polyglyceryl-3 Polyricinoleate, Polyhydroxystearic Acid, Potassium Sorbate, Proline, Purified Water, Rosa Canina (Rosehip) Fruit Oil, Sclerocarya Birrea (Marula) Seed Oil, Serine, Sodium Benzoate, Sodium Chloride, Sodium Hyaluronate, Sodium Lactate, Sodium PCA, Sorbitan Isostearate, Squalane, Threonine, Tocopheryl Acetate (Vitamin E), Valine, and Xanthan Gum

Questions?

Visit www.bluelizardsunscreen.com or call 800.877.8869

Crown Laboratories, Inc., Johnson City, TN 37604

Blue Lizard Sheer Lotion for Face - 1.7 fl oz Tube

BLUE LIZARD

AUSTRALIAN SUNSCREEN

50+

SHEER LOTION for face

MINERAL SUNSCREEN

UVA/UVB PROTECTION

BROAD SPECTRUM

SPF 50+

WATER RESISTANT (80 MINUTES)

P11901.00

Blue Lizard Sheer Lotion for face - 1.7 fl oz carton

BLUE LIZARD

AUSTRALIAN SUNSCREEN

50+

SHEER LOTION for face

MINERAL SUNSCREEN

BLUE LIGHT PROTECTION

UVA/UVB PROTECTION

BROAD SPECTRUM SPF 50+

WATER RESISTANT (80 MINUTES)

P11900.01